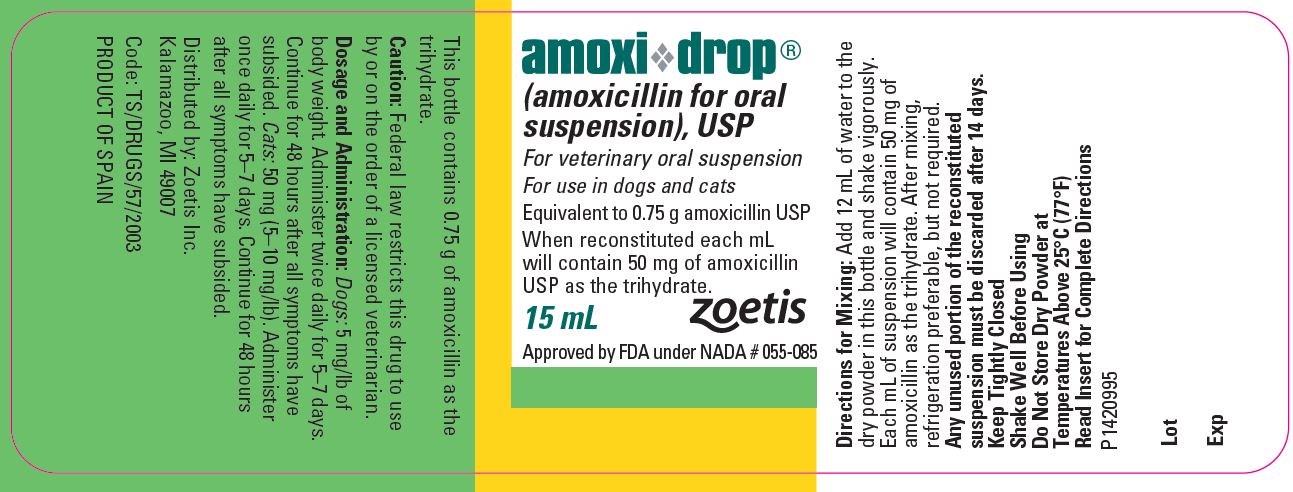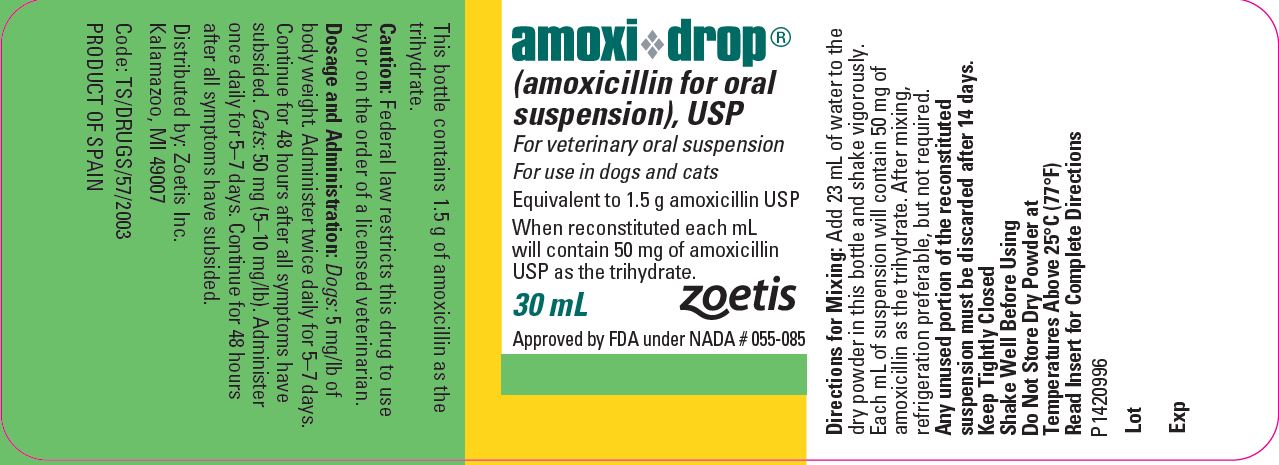 DRUG LABEL: Amoxi-Drop
NDC: 54771-6036 | Form: SUSPENSION
Manufacturer: Zoetis Inc.
Category: animal | Type: PRESCRIPTION ANIMAL DRUG LABEL
Date: 20241114

ACTIVE INGREDIENTS: AMOXICILLIN 50 mg/1 mL

amoxi-drop®
(amoxicillin)

Amoxi-Drop

(amoxicillin for oral suspension), USP

For veterinary oral suspension

For use in dogs and cats

CAUTION

Federal law restricts this drug to use by or on the order of a licensed veterinarian.

DESCRIPTION

Amoxi-Drop (amoxicillin for oral suspension), USP is a semisynthetic antibiotic with a broad spectrum of activity. It provides bactericidal activity against a wide range of common gram-positive and gram-negative pathogens. Chemically, it is D(-)-α-amino-p-hydroxybenzyl penicillin trihydrate.

CLINICAL PHARMACOLOGY

Amoxi-Drop is stable in the presence of gastric acid and may be given without regard to meals. It is rapidly absorbed after oral administration. It diffuses readily into most body tissues and fluids with the exception of brain and spinal fluid, except when meninges are inflamed. Most of the amoxicillin is excreted unchanged in the urine.

Amoxicillin is similar to ampicillin in its bactericidal action against susceptible organisms. It acts through the inhibition of biosynthesis of cell wall mucopeptide. In vitro and/or in vivo studies have demonstrated the susceptibility of most strains of the following gram-positive and gram-negative bacteria: α- and β-haemolytic streptococci, nonpenicillinase-producing staphylococci, Streptococcus faecalis, Escherichia coli, and Proteus mirabilis. Because it does not resist destruction by penicillinase, it is not effective against penicillinase-producing bacteria, particularly resistant staphylococci. All strains of Pseudomonas and most strains of Klebsiella and Enterobacter are resistant.

INDICATIONS

Dogs

Amoxi-Drop is indicated in the treatment of susceptible strains of the organisms causing the following infections:

Respiratory tract infections (tonsillitis, tracheobronchitis) due to Staphylococcus aureus, Streptococcus spp., E. coli, and Proteus mirabilis.

Genitourinary tract infections (cystitis) due to Staphylococcus aureus, Streptococcus spp., E. coli, and Proteus mirabilis.

Gastrointestinal tract infections (bacterial gastroenteritis) due to Staphylococcus aureus, Streptococcus spp., E. coli, and Proteus mirabilis.

Bacterial dermatitis due to Staphylococcus aureus, Streptococcus spp., and Proteus mirabilis.

Soft tissue infections (abscesses, lacerations, and wounds) due to Staphylococcus aureus, Streptococcus spp., E. coli, and Proteus mirabilis.

Cats

Amoxi-Drop is indicated in the treatment of susceptible strains of the organisms causing the following infections:

Upper respiratory tract infections due to Staphylococcus aureus, Staphylococcus spp., Streptococcus spp., Haemophilus spp., E. coli, Pasteurella spp., and Proteus mirabilis.

Genitourinary tract infections (cystitis) due to Staphylococcus aureus, Streptococcus spp., E. coli, Proteus mirabilis, and Corynebacterium spp.

Gastrointestinal tract infections due to E. coli, Proteus spp., Staphylococcus spp., and Streptococcus spp.

Skin and soft tissue infections (abscesses, lacerations, and wounds) due to Staphylococcus aureus, Staphylococcus spp., Streptococcus spp., E. coli, and Pasteurella multocida.

CONTRAINDICATIONS

The use of this drug is contraindicated in animals with a history of an allergic reaction to penicillin.

WARNINGS

For use in dogs and cats only. Not for use in animals which are raised for food production.

ADVERSE REACTIONS

Amoxicillin is a semisynthetic penicillin and has the potential for producing allergic reactions. If an allergic reaction occurs, administer epinephrine and/or steroids.

DOSAGE AND ADMINISTRATION

Dogs

The recommended dosage is 5 mg/lb of body weight. Administer twice daily for 5–7 days. Continue for 48 hours after all symptoms have subsided.

Cats

The recommended dosage is 50 mg (5–10 mg/lb). Administer once daily for 5–7 days. Continue for 48 hours after all symptoms have subsided.

Directions for Mixing Oral Suspension:

Add required amount of water (see following table) to the bottle and shake vigorously. Each mL of suspension will contain 50 mg of amoxicillin as the trihydrate.

Bottle Size | Amount of Water Required for Reconstitution
15 mL | 12 mL
30 mL | 23 mL

Note: Any unused portion of the reconstituted suspension must be discarded after 14 days. After mixing, refrigeration preferable, but not required.

STORAGE AND HANDLING

Do Not Store Dry Powder at Temperatures Above 25°C (77°F)

HOW SUPPLIED

Amoxi-Drop is supplied in 15-mL bottles containing 0.75 g and 30-mL bottles containing 1.5 g of amoxicillin activity. When reconstituted with required amount of water, each mL contains 50 mg of amoxicillin as the trihydrate.

Approved by FDA under NADA # 055-085
PRODUCT OF SPAIN
zoetis
Distributed by:
Zoetis Inc.
Kalamazoo, MI 49007

Revised: February 2019
P1518394